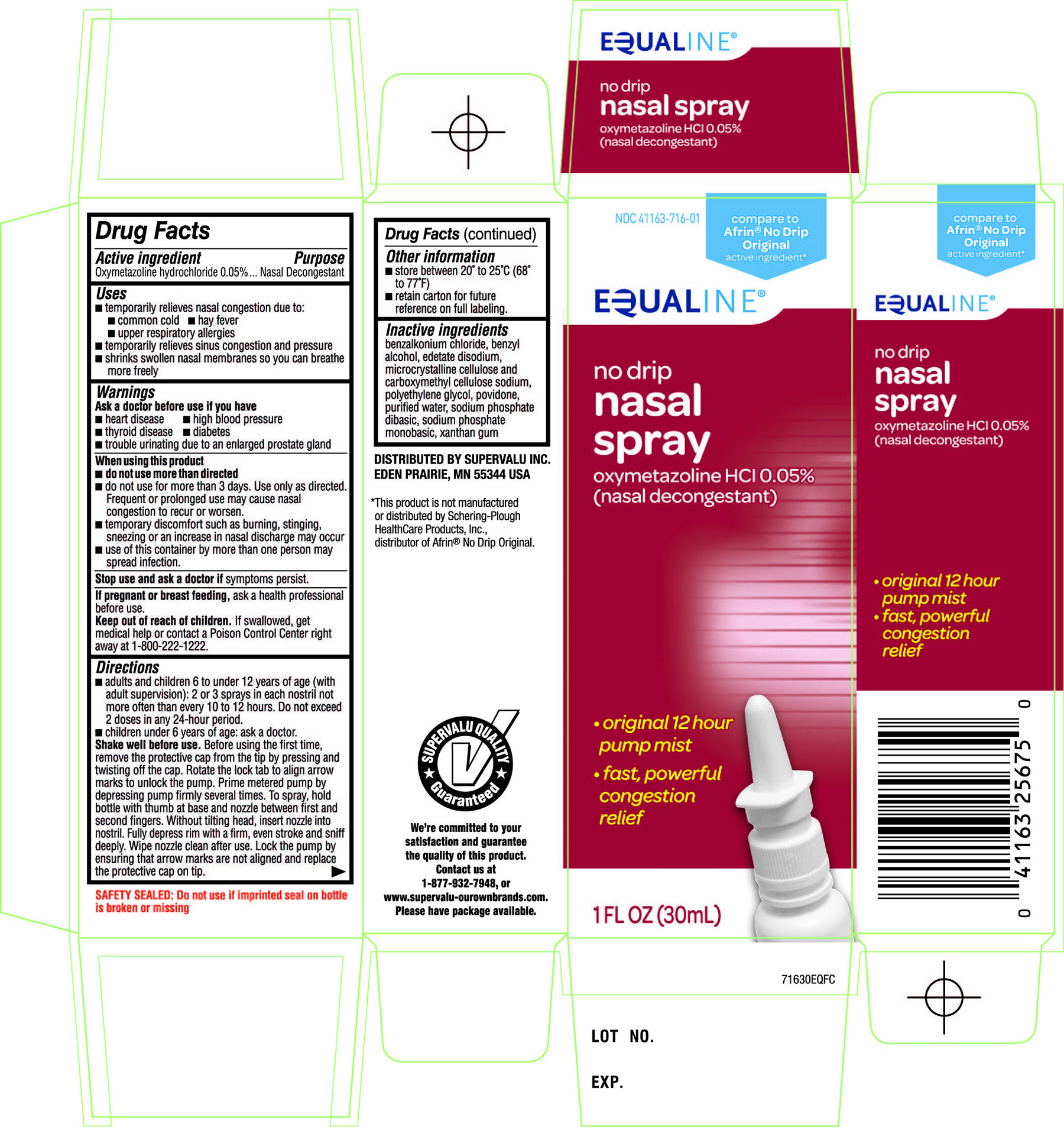 DRUG LABEL: EQUALINE Oxymetazoline HCl Nasal Decongestant
NDC: 41163-716 | Form: SPRAY
Manufacturer: SUPERVALU INC
Category: otc | Type: HUMAN OTC DRUG LABEL
Date: 20171227

ACTIVE INGREDIENTS: OXYMETAZOLINE HYDROCHLORIDE 0.05 g/100 mL
INACTIVE INGREDIENTS: BENZALKONIUM CHLORIDE; BENZYL ALCOHOL; EDETATE DISODIUM; CELLULOSE, MICROCRYSTALLINE; CARBOXYMETHYLCELLULOSE SODIUM; POLYETHYLENE GLYCOLS; POVIDONES; WATER; SODIUM PHOSPHATE, DIBASIC, ANHYDROUS; SODIUM PHOSPHATE, MONOBASIC, ANHYDROUS; XANTHAN GUM

Active ingredient

Oxymetazoline hydrochloride 0.05%

Purpose

Nasal Decongestant

Uses

- temporarily relieves nasal congestion due to:
- common cold
- hay fever
- upper respiratory allergies
- temporarily relieves sinus congestion and pressure
- shrinks swollen nasal membranes so you can breathe more freely.

Warnings

Ask a doctor before use if you have

- heart disease
- high blood pressure
- thyroid disease
- diabetes
- trouble urinating due to an enlarged prostate gland

When using this product

- do not use more than directed
- do not use for more than 3 days. Use only as directed. Frequent or prolonged use may cause nasal congestion to recur or worsen.
- temporary discomfort such as burning, stinging, sneezing or an increase in nasal discharge may occur
- use of this container by more than one person may spread infection.

Stop use and ask a doctor if

symptoms persist.

If pregnant or breast-feeding,

ask a health professional before use.

Keep out of reach of children.

If swallowed, get medical help or contact a Poison Control Center right away at 1-800-222-1222.

Directions

- adults and children 6 to under 12 years of age (with adult supervision): 2 or 3 sprays in each nostril not more often than every 10 to 12 hours. Do not exceed 2 doses in any 24-hour period.
- children under 6 years of age: ask a doctor.

Shake well before use. Before using the first time, remove the protective cap from the tip by pressing and twisting off the cap. Rotate the lock tab to align arrow marks to unlock the pump. Prime metered pump by depressing pump firmly several times. To spray, hold bottle with thumb at base and nozzle between first and second fingers. Without tilting head, insert nozzle into nostril. Fully depress rim with a firm, even stroke and sniff deeply. Wipe nozzle clean after use. Lock the pump by ensuring that arrow marks are not aligned and replace the protective cap on tip.

Other information

- store between 20°to 25°C (68°to77°F)
- retain carton for future reference on full labeling.

Inactive ingredients

benzalkonium chloride, benzyl alcohol, edetate disodium, microcrystalline cellulose and carboxymethyl cellulose sodium, polyethylene glycol, povidone, purified water, sodium phosphate dibasic, sodium phosphate monobasic, xanthan gum.

Principal Display Panel

NDC 41163-716-01

compare to Afrin® No-Drip Original active ingredient*

EQUALINE®

no drip

nasal spray

Oxymetazoline HCl 0.05%

(nasal decongestant)

- original 12 hour pump mist
- fast, powerful congestion relief

1 FL OZ (30 mL)

SAFETY SEALED: Do not use if imprinted seal on bottle is broken or missing

DISTRIBUTED BY SUPERVALU INC.

EDEN PRAIRIE, MN 55344 USA

*This product is not manufactured or distributed by Schering-Plough Healthcare Products, Inc., distributor of Afrin®No Drip Original.

SUPERVALU QUALITY Guaranteed

We’re committed to your satisfaction and guarantee the quality of this product.

Contact us at 1-877-932-7948, or

www.supervalu-ourownbrands.com.

Please have package available.